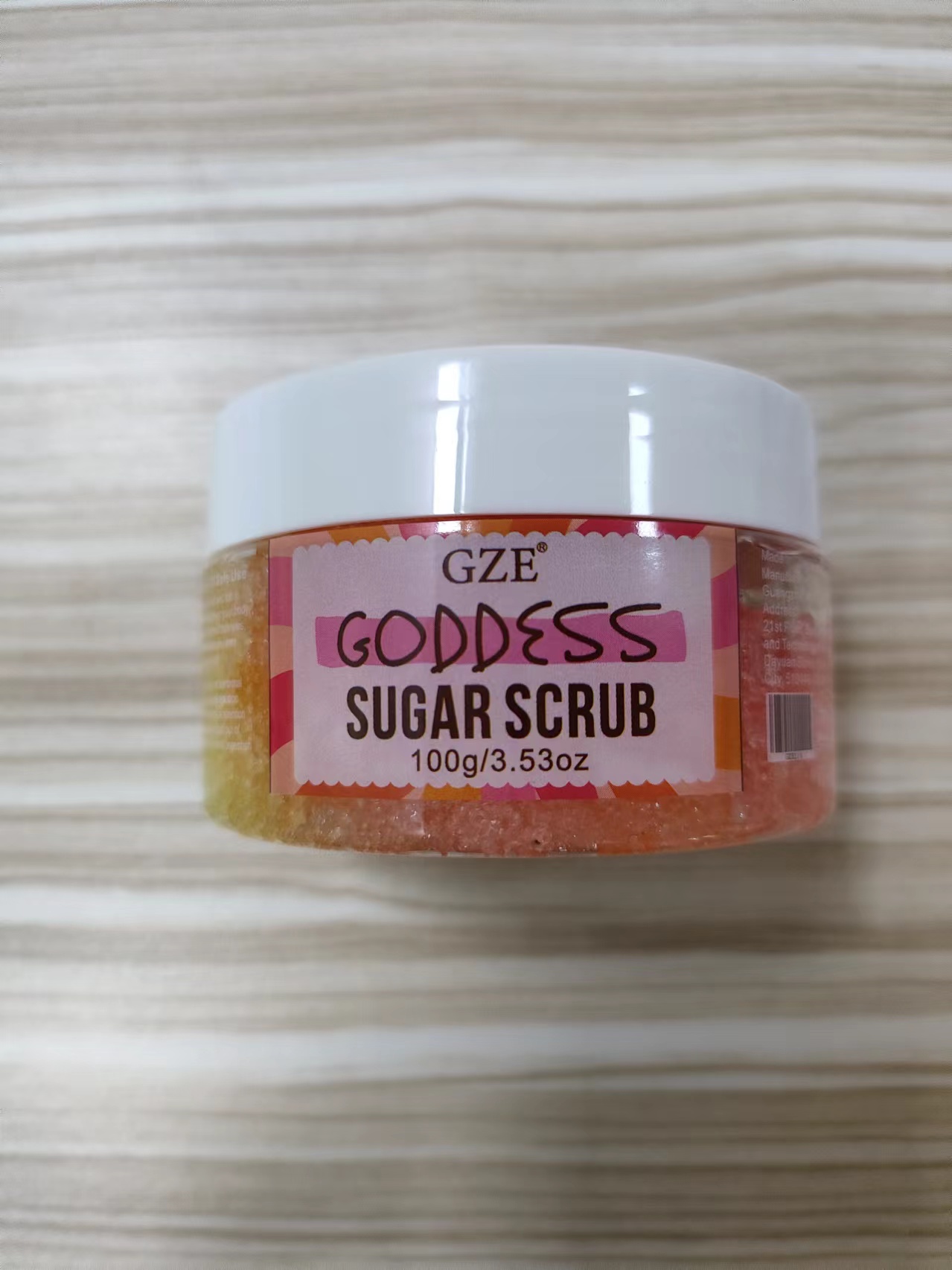 DRUG LABEL: GZE GODDESS SUGAR SCRUB
NDC: 74458-217 | Form: GRANULE
Manufacturer: Guangzhou Yilong Cosmetics Co., Ltd
Category: otc | Type: HUMAN OTC DRUG LABEL
Date: 20241122

ACTIVE INGREDIENTS: SUCROSE 15 g/100 g
INACTIVE INGREDIENTS: POLYSORBATE 20; AQUA; LIMONENE, (+)-; SODIUM SULFATE; SILICA; CI 19140; GLYCERIN; CI 17200; SODIUM CHLORIDE; CI 14700

GZE GODDESS SUGAR SCRUB

ACTIVE INGREDIENT

Sucrose

INACTIVE INGREDIENT

Glycerin

Sodium Chloride

Sodium Sulfate

Silica

Polysorbate 20

Aqua

Parfum

CI 19140

CI 14700

CI 17200

Limonene

PURPOSE

Exfoliating.

WARNINGS

For external use only.

INDICATIONS AND USAGE

Massage onto skin using circular motions
starting with any sore muscles or cellulite.the legs, then arms &
body, making your way bock toward your heart. Rinse well

Stop use and ask a doctor if rash occurs.

Do not use on damaged or broken skin.

When using this product keep out of eyes. Rinse with water to remove.

Keep out of reach of children. If swallowed, get medical help or contact a Poison Control Center right away.

DOSAGE AND ADMINISTRATION

Massage onto skin using circular motions
starting with any sore muscles or cellulite.the legs, then arms &
body, making your way bock toward your heart. Rinse well